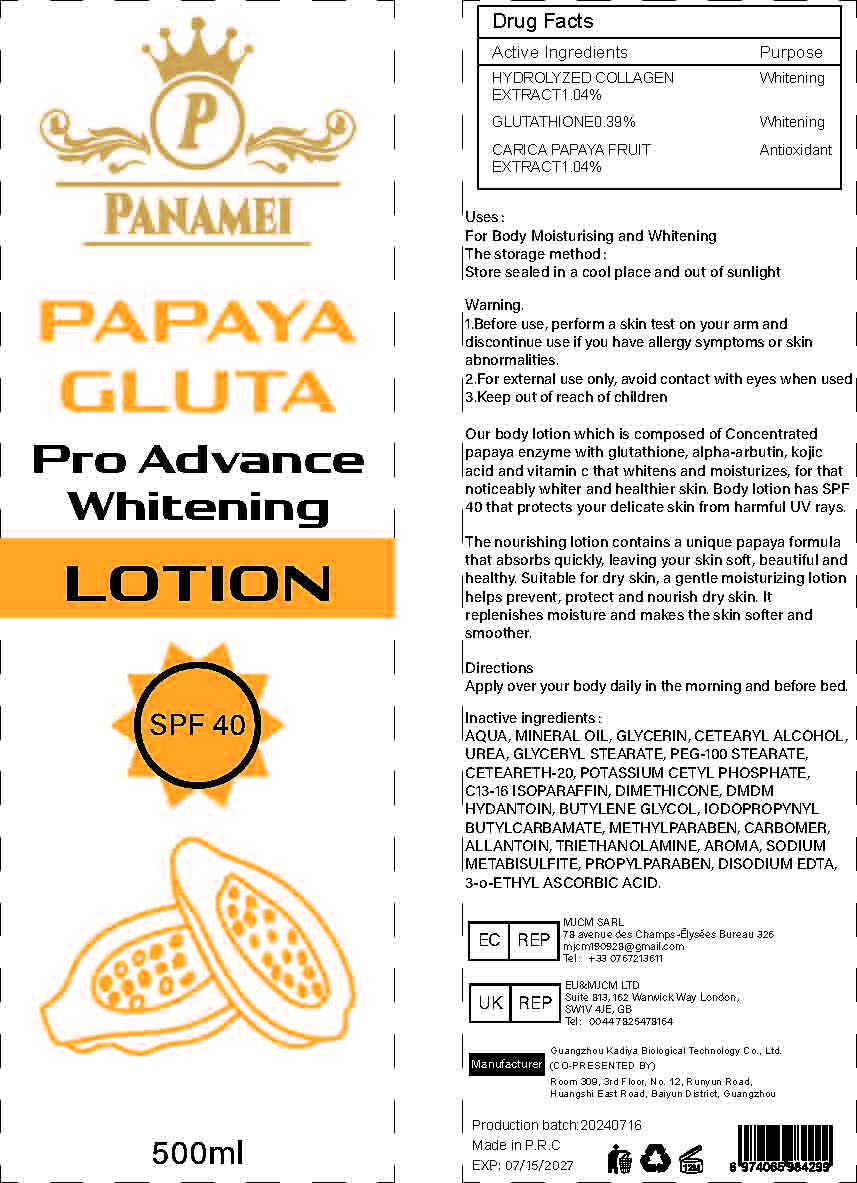 DRUG LABEL: Papaya Whitening BodyLotion
NDC: 84423-025 | Form: EMULSION
Manufacturer: Guangzhou Kadiya Biotechnology Co., Ltd.
Category: otc | Type: HUMAN OTC DRUG LABEL
Date: 20240723

ACTIVE INGREDIENTS: GLUTATHIONE 1.95 mg/500 mL; PAPAYA 5.2 mg/500 mL
INACTIVE INGREDIENTS: SODIUM METABISULFITE; BUTYLENE GLYCOL; CARBOXYPOLYMETHYLENE; UREA; C13-16 ISOPARAFFIN; CETOSTEARYL ALCOHOL; PROPYLPARABEN; EDETATE DISODIUM; POLYOXYL 20 CETOSTEARYL ETHER; POTASSIUM CETYL PHOSPHATE; METHYLPARABEN; WATER; PEG-100 STEARATE; DIMETHICONE; IODOPROPYNYL BUTYLCARBAMATE; ALLANTOIN; 3-O-ETHYL ASCORBIC ACID; GLYCERIN; DMDM HYDANTOIN; TROLAMINE; GLYCERYL MONOSTEARATE; MINERAL OIL

Uses：
For Body Moisturising and Whitening

INACTIVE INGREDIENT

AQUA、MINERAL OIL、GLYCERIN、CETEARYL ALCOHOL、UREA、GLYCERYL STEARATE、PEG-100 STEARATE、CETEARETH-20、POTASSIUM CETYL PHOSPHATE、C13-16 ISOPARAFFIN、DIMETHICONE、DMDM HYDANTOIN、BUTYLENE GLYCOL、IODOPROPYNYL BUTYLCARBAMATE、METHYLPARABEN、CARBOMER、ALLANTOIN、TRIETHANOLAMINE、AROMA、SODIUM METABISULFITE、PROPYLPARABEN、DISODIUM EDTA、3-o-ETHYL ASCORBIC ACID

Warning.
1.Before use, perform a skin test on your arm and discontinue use if you have allergy symptoms or skin abnormalities.
2、For external use only, avoid contact with eyes when used
3、Keep out of reach of children

INDICATIONS AND USAGE

Apply over your body daily in the morning and before bed

KEEP OUT OF REACH OF CHILDREN SECTION

Active Ingredients
HYDROLYZED COLLAGEN EXTRACT 1.04%
GLUTATHIONE 0.39%
CARICA PAPAYA FRUIT EXTRACT 1.04%

DOSAGE AND ADMINISTRATION

Apply over your body daily in the morning and before bed.

PACKAGE LABEL

Active Ingredients
HYDROLYZED COLLAGEN EXTRACT 1.04%
GLUTATHIONE 0.39%
CARICA PAPAYA FRUIT EXTRACT 1.04%
Uses：
For Body Moisturising and Whitening
The storage method：
Store sealed in a cool place and out of sunlight
Warning.
1.Before use, perform a skin test on your arm and discontinue use if you have allergy symptoms or skin abnormalities.
2、For external use only, avoid contact with eyes when used
3、Keep out of reach of children
Inactive ingredients：
AQUA、MINERAL OIL、GLYCERIN、CETEARYL ALCOHOL、UREA、GLYCERYL STEARATE、PEG-100 STEARATE、CETEARETH-20、POTASSIUM CETYL PHOSPHATE、C13-16 ISOPARAFFIN、DIMETHICONE、DMDM HYDANTOIN、BUTYLENE GLYCOL、IODOPROPYNYL BUTYLCARBAMATE、METHYLPARABEN、CARBOMER、ALLANTOIN、TRIETHANOLAMINE、AROMA、SODIUM METABISULFITE、PROPYLPARABEN、DISODIUM EDTA、3-o-ETHYL ASCORBIC ACID